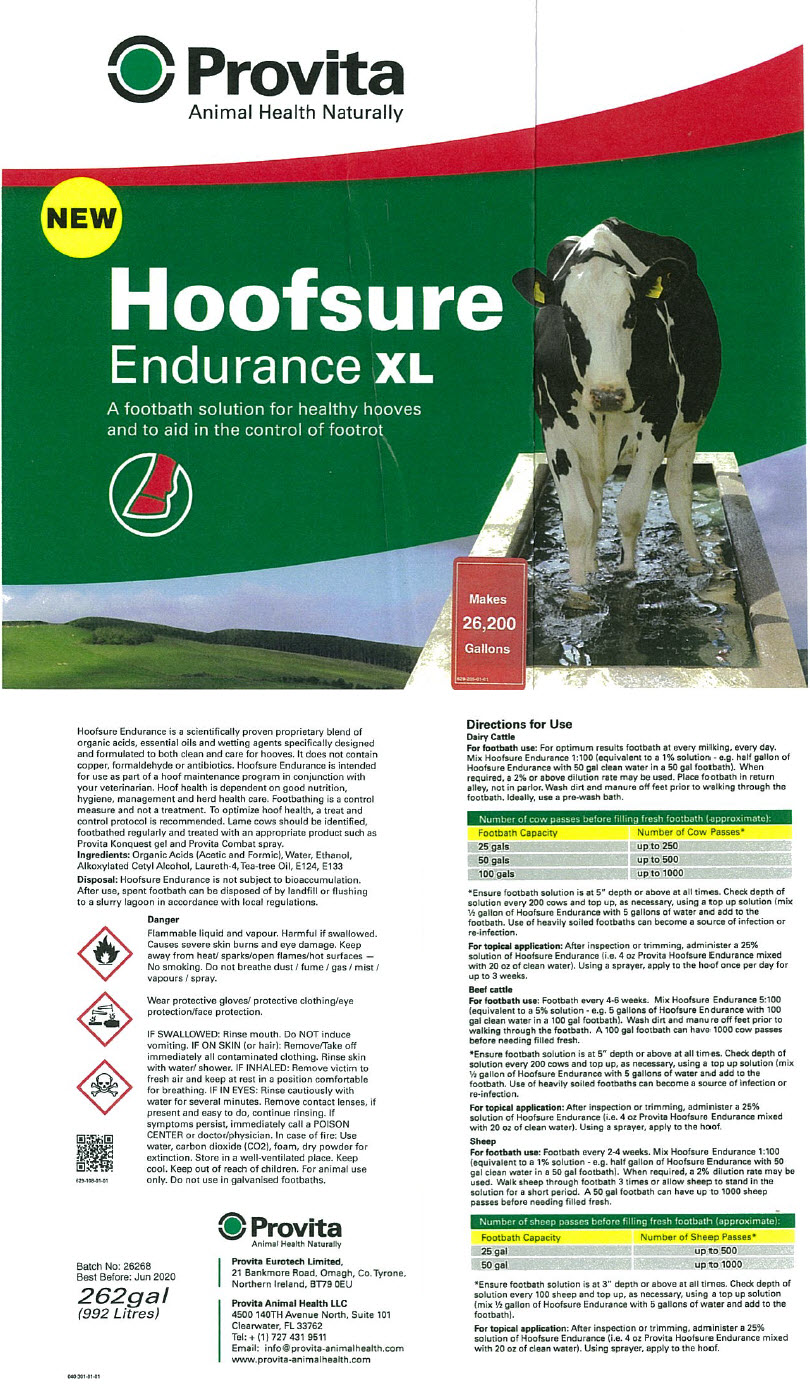 DRUG LABEL: Provita Hoofsure Endurance XL
NDC: 16371-106 | Form: SOLUTION, CONCENTRATE
Manufacturer: Provita Eurotech Ltd
Category: animal | Type: OTC ANIMAL DRUG LABEL
Date: 20181011

ACTIVE INGREDIENTS: FORMIC ACID 608 g/1 L
INACTIVE INGREDIENTS: CETYL ALCOHOL; LAURETH-4

Provita Hoofsure Endurance XL

VETERINARY INDICATIONS

Hoofsure Endurance is a scientifically proven proprietary blend of organic acids, essential oils and wetting agents specifically designed and formulated to both clean and care for hooves. It is safe, non-toxic, biodegradable and does not contain copper, formaldehyde or antibiotics.

Hoofsure Endurance is intended for use as part of a hoof maintenance program in conjunction with your veterinarian. Hoof health is dependent on good nutrition, hygiene, management and herd health care. Footbathing is a control measure and not a treatment. To optimize hoof health, a treat and control protocol is recommended. Lame cows should be identified, footbathed regularly and treated with an appropriate product such as Provita Konquest gel and Provita Combat spray.

Ingredients

Organic Acids (Acetic and Formic), Water, Ethanol, Alkoxylated Cetyl Alcohol, Laureth-4, Tea-tree Oil, E124, E133

Disposal

Hoofsure Endurance is environmentally friendly. After use, spent footbath can be disposed of by landfill or flushing to a slurry lagoon in accordance with local regulations.

Precautions

Do not use in galvanised footbaths.

Care must be taken when handling undiluted product.

Wear suitable protective clothing and eye protection.

Do not breathe vapour.

Contains Formic Acid.

Causes burns.

In case of contact with eyes, rinse immediately with plenty of water and seek medical advice.

Keep out of reach of children.

See Health and Safety Data Sheet.

Directions for Use

DAIRY CATTLE For footbath use: For optimum results footbath at every milking, every day. Mix Hoofsure Endurance 1:100 (equivalent to a 1% solution - e.g. half gallon of Hoofsure Endurance with 50 gal clean water in a 50 gal footbath). When required, a 2% or above dilution rate may be used. Place footbath in return alley, not in parlor. Wash dirt and manure off feet prior to walking through the footbath. Ideally, use a pre-wash bath.

Number of cow passes before filling fresh footbath (approximate):
Footbath Capacity | Number of Cow Passes [Ensure footbath solution is at 5" depth or above at all times. Check depth of solution every 200 cows and top up, as necessary, using a top up solution (mix ½ gallon of Hoofsure Endurance with 5 gallons of water and add to the footbath. Use of heavily soiled footbaths can become a source of infection or re-infection.]
25 gals | up to 250
50 gals | up to 500
100 gals | up to 1000

For topical application: After inspection or trimming, administer a 25% solution of Hoofsure Endurance (i.e. 4 oz Provita Hoofsure Endurance mixed with 20 oz of clean water). Using a sprayer, apply to the hoof once per day for up to 3 weeks.

BEEF CATTLE For footbath use: Footbath every 4-6 weeks. Mix Hoofsure Endurance 5:100 (equivalent to a 5% solution - e.g. 5 gallons of Hoofsure Endurance with 100 gal clean water in a 100 gal footbath). Wash dirt and manure off feet prior to walking through the footbath. A 100 gal footbath can have 1000 cow passes before needing filled fresh.

*Ensure footbath solution is at 5" depth or above at all times. Check depth of solution every 200 cows and top up, as necessary, using a top up solution (mix ½ gallon of Hoofsure Endurance with 5 gallons of water and add to the footbath. Use of heavily soiled footbaths can become a source of infection or re-infection.

For topical application: After inspection or trimming, administer a 25% solution of Hoofsure Endurance (i.e. 4 oz Provita Hoofsure Endurance mixed with 20 oz of clean water). Using a sprayer, apply to the hoof.

SHEEP For footbath use: Footbath every 2-4 weeks. Mix Hoofsure Endurance 1:100 (equivalent to a 1% solution - e.g. half gallon of Hoofsure Endurance with 50 gal clean water in a 50 gal footbath). When required, a 2% dilution rate may be used. Walk sheep through footbath 3 times or allow sheep to stand in the solution for a short period. A 50 gal footbath can have up to 1000 sheep passes before needing filled fresh.

Number of sheep passes before filling fresh footbath (approximate):
Footbath Capacity | Number of Sheep Passes [Ensure footbath solution is at 3" depth or above at all times. Check depth of solution every 100 sheep and top up, as necessary, using a top up solution (mix ½ gallon of Hoofsure Endurance with 5 gallons of water and add to the footbath).]
25 gal | up to 500
50 gal | up to 1000

For topical application: After inspection or trimming, administer a 25% solution of Hoofsure Endurance (i.e. 4 oz Provita Hoofsure Endurance mixed with 20 oz of clean water). Using sprayer, apply to the hoof.

1.25gal
(4.75 Litres)

Provita Eurotech Limited,
21 Bankmore Road, Omagh, Co. Tyrone,
Northern Ireland, BT79 0EU
Provita Animal Health LLC
4500 140TH Avenue North, Suite 101
Clearwater, FL 33762
Tel: + (1) 727 431 9511
Email: info@provita-animalhealth.com

www.provita-animalhealth.com

PRINCIPAL DISPLAY PANEL - 992 Litre Drum Label

Provita
Animal Health Naturally

NEW

Hoofsure
Endurance XL

A footbath solution for healthy hooves
and to aid in the control of footrot

Makes
26,200
Gallons